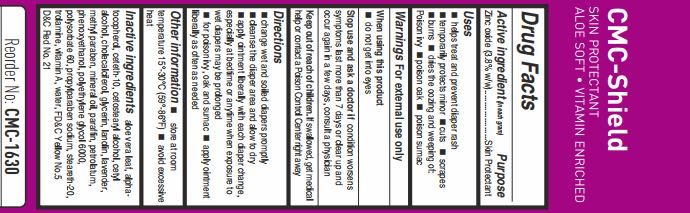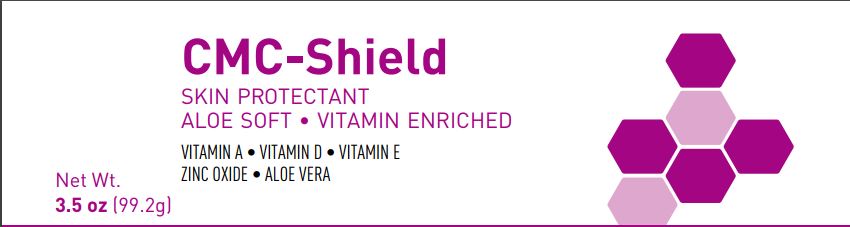 DRUG LABEL: CMC SHIELD SKIN PROTECTANT
NDC: 71168-3066 | Form: CREAM
Manufacturer: SKYLARK CMC PRIVATE LIMITED
Category: otc | Type: HUMAN OTC DRUG LABEL
Date: 20170912

ACTIVE INGREDIENTS: ZINC OXIDE 3.8 g/100 g
INACTIVE INGREDIENTS: ALPHA-TOCOPHEROL; METHYLPARABEN; PARAFFIN; PETROLATUM; POLYETHYLENE GLYCOL 6000; STEARETH-20; TROLAMINE; VITAMIN A; WATER; D&C RED NO. 21; CETYL ALCOHOL; LAVENDER OIL; PROPYLPARABEN SODIUM; FD&C YELLOW NO. 5; CETETH-10; CETOSTEARYL ALCOHOL; LANOLIN; MINERAL OIL; ALOE VERA LEAF; CHOLECALCIFEROL; GLYCERIN; PHENOXYETHANOL; POLYSORBATE 60

CMC-SHIELD

ACTIVE INGREDIENT

Zinc Oxide (3.8%)

PURPOSE

Skin Protectant

USES

- helps treat and prevent diaper rash
- temporarily protects from minor cuts, scrapes
- burns dries the oozing and weeping of poison ivy, poison oak, poison sumac

WARNINGS

For external use only

WHEN USING THIS PRODUCT

- do not get into eyes

STOP USE AND ASK A DOCTOR IF

Condition worsens or symptoms last more than 7 days or clear up and occur again in a few days, consult a physician

KEEP OUT OF REACH OF CHILDREN

If swallowed, get medical help or contact a Poison Control Center right away

DIRECTIONS

- change wet and soiled diapers promptly
- cleanse the diaper area and allow to dry
- apply ointment liberally with each diaper change, especially at bedtime or anytime when exposure to wet diapers may be prolonged
- for poison ivy, oak, and sumac
- apply ointment liberally as needed

OTHER INFORMATION

- Store at a room temperature 15-30° C (59-86 F)
- Avoid excessive heat

INACTIVE INGREDIENTS

aloe vera leaf, alpha-tocopherol, ceteth-10, cetostearyl alcohol, cetyl alcohol, cholecalciferol, glycerin, lanolin, lavender, methylparaben, mineral oil, paraffin, petrolatum, phenoxyethanol, polyethylene glycol 6000, polysorbate 60, propylparaben sodium, steareth-20, trolamine, vitamin-A, water, FDC Yellow No. 5, DC Red No.21